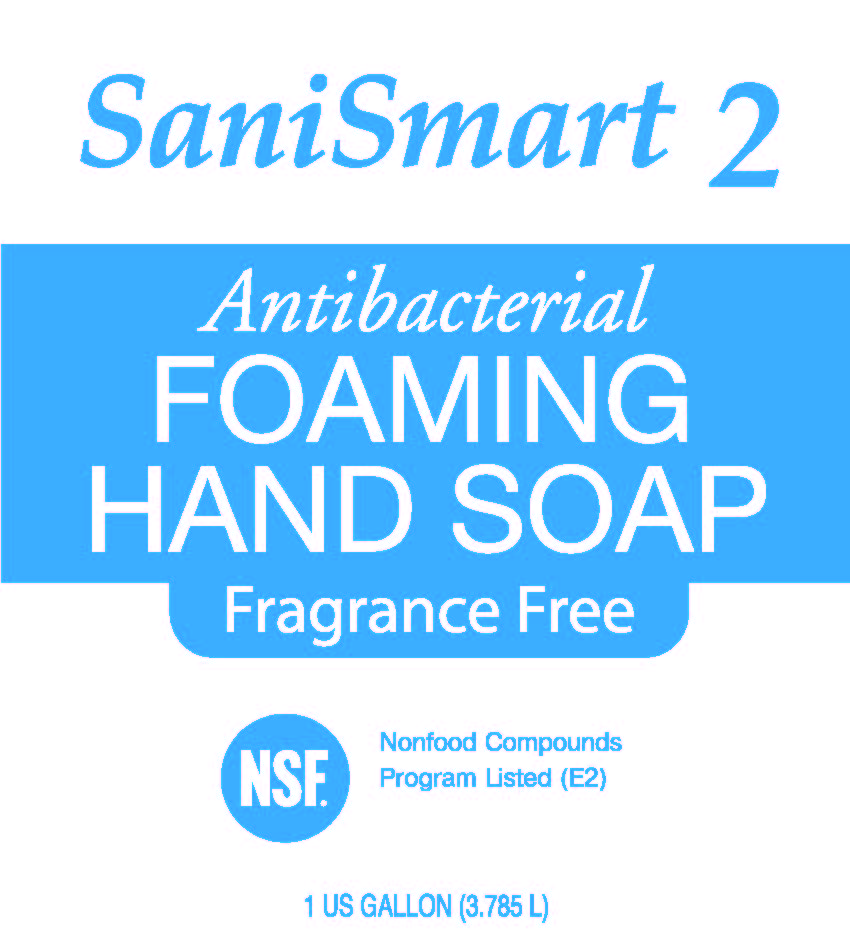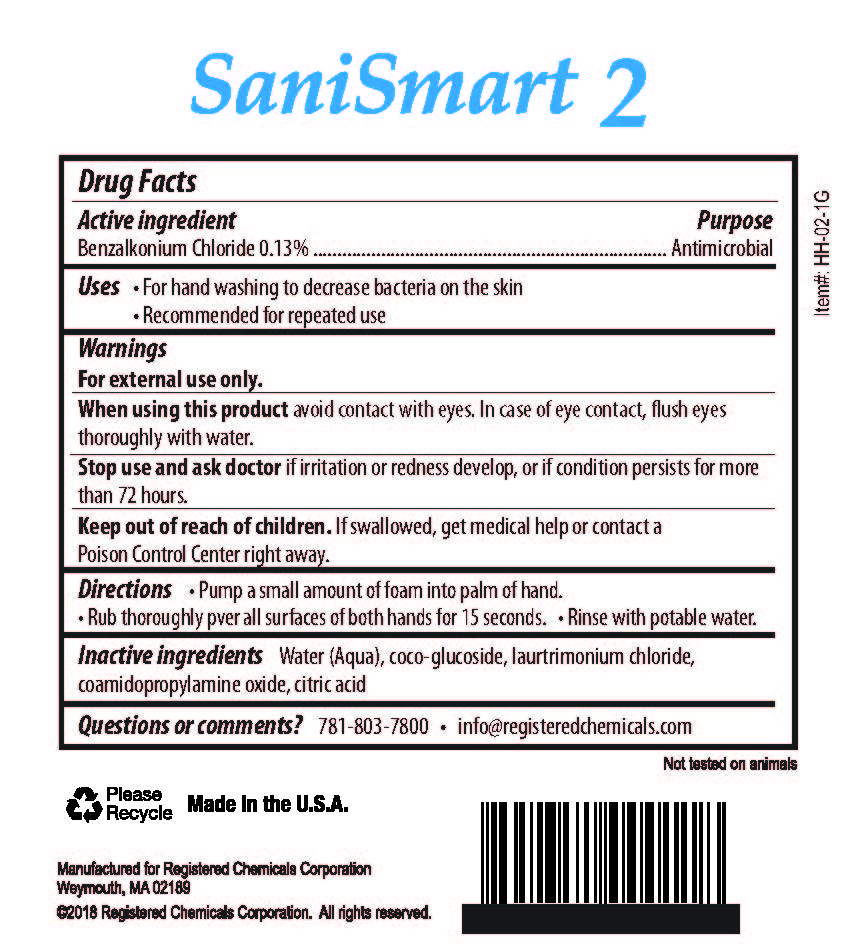 DRUG LABEL: SaniSmart 2
NDC: 72130-002 | Form: LIQUID
Manufacturer: Registered Chemicals Corporation
Category: otc | Type: HUMAN OTC DRUG LABEL
Date: 20180314

ACTIVE INGREDIENTS: BENZALKONIUM CHLORIDE .13 g/100 mL
INACTIVE INGREDIENTS: WATER; COCO GLUCOSIDE; LAURTRIMONIUM CHLORIDE; COCAMIDOPROPYLAMINE OXIDE; CITRIC ACID MONOHYDRATE

Active ingredient

Benzalkonium Chloride 0.13%

Purpose

Antimicrobial

INDICATIONS AND USAGE

Uses •For hand washing to decrease bacteria on the skin

•Recommended for repeated use

Warnings

For external use only.

When using this product avoid contact with eyes. In case of eye contact, flush eyes

thoroughly with water.

Stop use and ask a doctor if irritation or redness develop, or if condition persists for more

than 72 hours.

Keep out of reach of children. If swallowed, get medical help or contact a

Poison Control Center right away.

DOSAGE AND ADMINISTRATION

Directions •Pump a small amount of foam into palm of hand.

•Rub thoroughly over all surfaces of both hands for 15 seconds. •Rinse with potable water.

INACTIVE INGREDIENT

Inactive ingredients Water (Aqua), coco-glucoside, laurtrimonium chloride,

coamidopropylamine oxide, citric acid

Questions or comments? 781-803-7800 •info@registeredchemicals.com